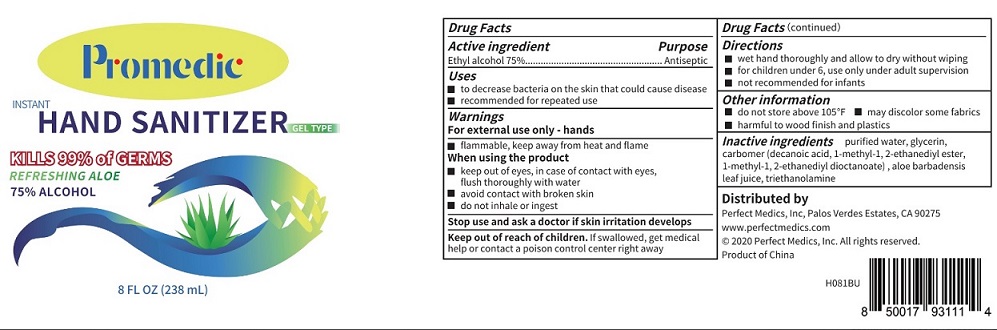 DRUG LABEL: Promedic
NDC: 79134-004 | Form: GEL
Manufacturer: Perfect Medics, Inc
Category: otc | Type: HUMAN OTC DRUG LABEL
Date: 20200708

ACTIVE INGREDIENTS: ALCOHOL 75 mL/100 mL
INACTIVE INGREDIENTS: WATER; GLYCERIN; CARBOMER HOMOPOLYMER TYPE A; ALOE VERA LEAF; TROLAMINE

Promedic HAND SANITIZER GEL TYPE

Active Ingredients

Ethyl alcohol 75%.

Purpose

Antiseptic

Warnings

For external use only - hands.

Flammable, keep away from heat and flame.

When using the product.

- keep out of eyes, in case of contact with eyes, flush thoroughly with water.
- avoid contact with broken skin.
- do not inhale or ingest.

Stop use and ask a doctor if skin irritation develops.

Uses

- to decrease bacteria on the skin that could cause disease.
- recommended for repeated use.

Directions

- Wet hand thoroughly and allow to dry without wiping.
- For children under 6, use only under adult supervision.
- not recommended for infants.

Keep Out of Reach of Children.

- If swallowed, get medical help or contact a poison control center right away.

Other Information

- do not store above 105F.
- may discolor some fabrics.
- harmful to wood finish and plastics.

Inactive Ingredients

Purified water, Glycerin, Carbomer (Decanoic acid, 1-methyl-1,2-ethanediyl ester mixed with 1-methyl-1,2-ethanediyl dioctanoate) , aloe barbadensis leaf juice, triethanolamine